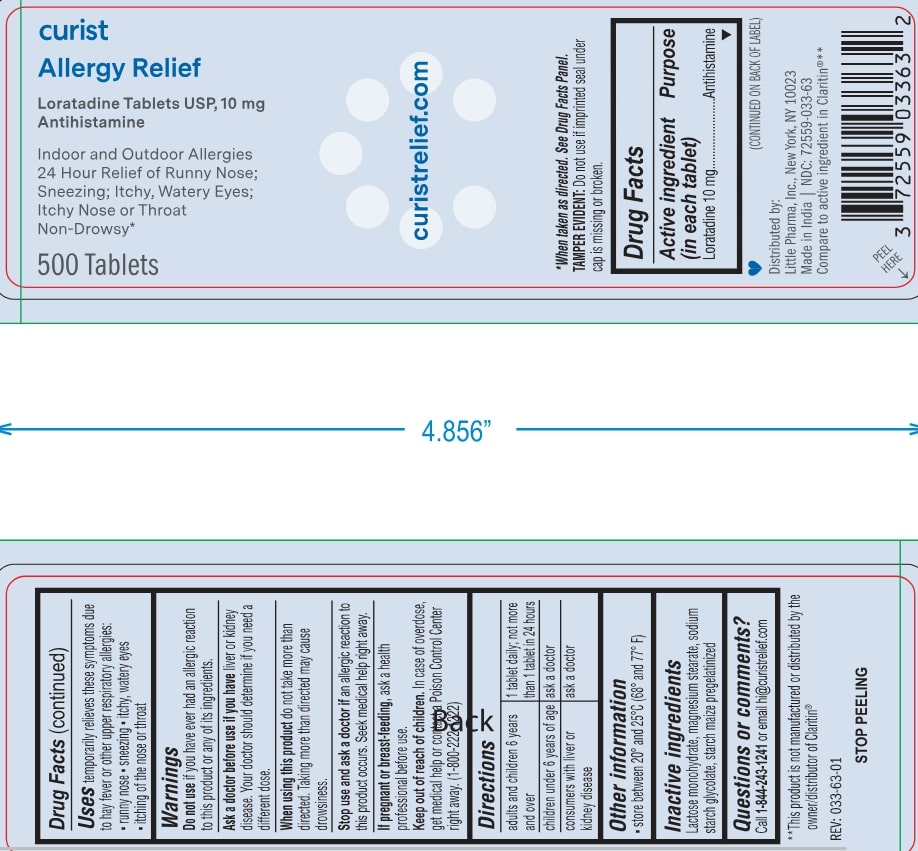 DRUG LABEL: Curist Allergy Relief
NDC: 72559-033 | Form: TABLET
Manufacturer: Little Pharma, Inc.
Category: otc | Type: HUMAN OTC DRUG LABEL
Date: 20250615

ACTIVE INGREDIENTS: LORATADINE 10 mg/1 1
INACTIVE INGREDIENTS: SODIUM STARCH GLYCOLATE TYPE A POTATO; LACTOSE MONOHYDRATE; MAGNESIUM STEARATE; STARCH, CORN

Drug Facts

Active ingredient (in each tablet)

Loratadine 10 mg

Purpose

Antihistamine

Uses

temporarily relieves these symptoms due to hay fever or other upper respiratory allergies:

- runny nose
- sneezing
- itchy, watery eyes
- itching of the nose or throat

Warnings

Do not use if you have ever had an allergic reaction to this product or any of its ingredients.

Ask a doctor before use if you have liver or kidney disease. Your doctor should determine if you need a different dose.

When using this product do not take more than directed. Taking more than directed may cause drowsiness.

Stop use and ask a doctor if an allergic reaction to this product occurs. Seek medical help right away.

PREGNANCY OR BREAST FEEDING

If pregnant or breast-feeding, ask a health professional before use.

Keep out of reach of children. In case of overdose, get medical help or contact a Poison Control Center right away. (1-800-222-1222)

Directions

adults and children 6 years and over | 1 tablet daily; not more than 1 tablet in 24 hours
children under 6 years of age | ask a doctor
consumers with liver or kidney disease | ask a doctor

Other information

- store between 20° and 25°C (68° and 77° F)

Inactive ingredients

Lactose monohydrate, magnesium stearate, sodium starch glycolate, starch maize pregelatinized

Questions or comments?

Call 1-844-243-1241 or email hi@curistrelief.com

curistrelief.com

*When taken as directed. See Drug Facts Panel.
TAMPER EVIDENT: Do not use if imprinted seal under cap is missing or broken.

(CONTINUED ON BACK OF LABEL)

Distributed by: Little Pharma, Inc., New York, NY 10023
Made in India | NDC: 72559-033-48
Compare to active ingredient in Claritin®**

PEEL HERE

**This product is not manufacutred or distributed by the owner/distributor of Claritin®

REV: 033-48-01

STOP PEELING

PACKAGE LABEL

curist

Allergy Relief

Loratadine Tablets USP, 10 mg

Antihistamine

Indoor and Outdoor Allergies
24 Hour Relief of Runny Nose;
Sneezing; Itchy, Watery Eyes;
Itchy Nose or Throat
Non-Drowsy*

500 Tablets